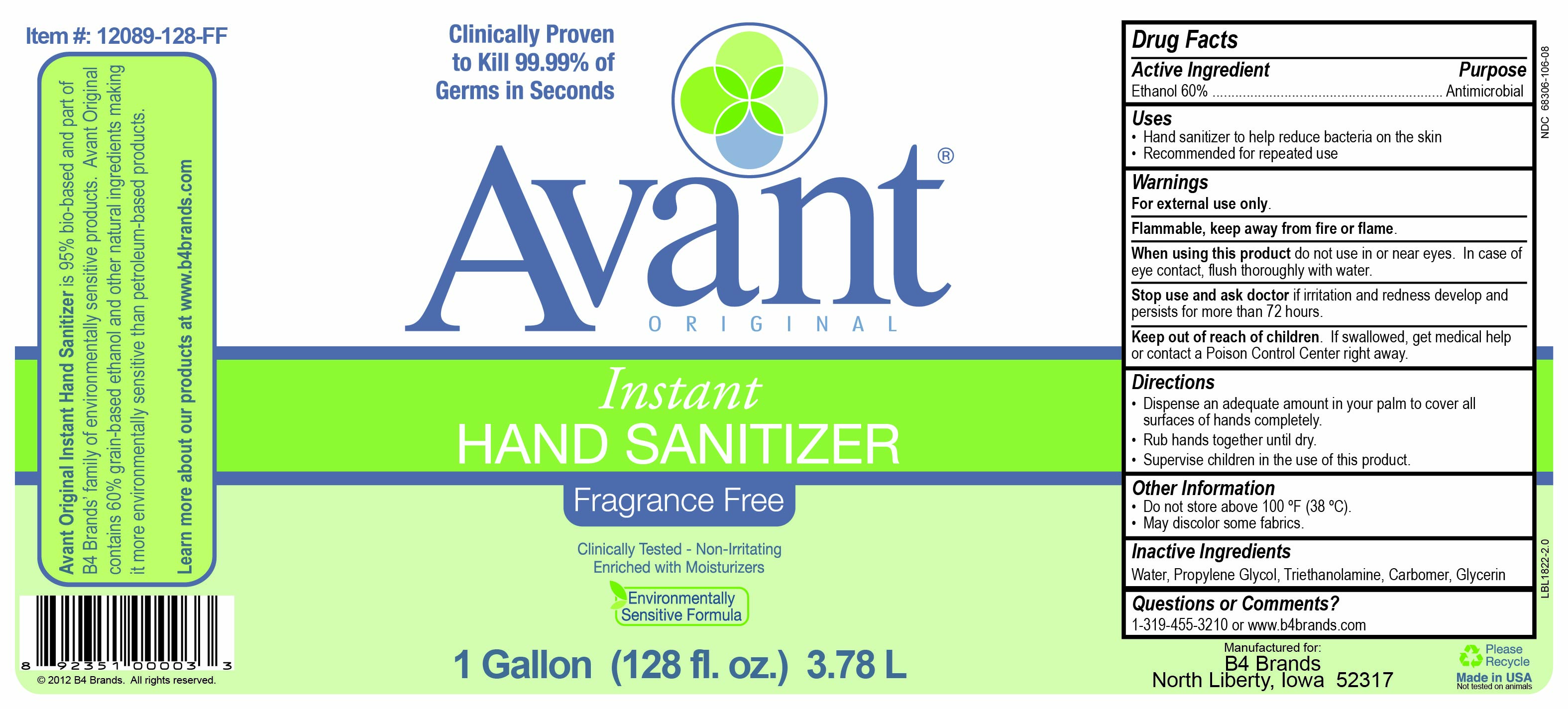 DRUG LABEL: Avant Original - Fragrance Free
NDC: 68306-106 | Form: GEL
Manufacturer: B4 Soap LLC
Category: otc | Type: HUMAN OTC DRUG LABEL
Date: 20260226

ACTIVE INGREDIENTS: ALCOHOL 60 mL/100 mL
INACTIVE INGREDIENTS: WATER; GLYCERIN; TROLAMINE; CARBOMER INTERPOLYMER TYPE A (ALLYL SUCROSE CROSSLINKED); PROPYLENE GLYCOL

B4 Brands: Avant Original - Fragrance Free Instant Hand Sanitizer

Active Ingredient

Ethanol 60%

Purpose

Antimicrobial

Uses

- Hand sanitizer to help reduce bacteria on the skin
- Recommended for repeated use

Warnings

For external use only.

Flammable, keep away from fire or flame.

When using this product do not use in or near eyes. In case of eye contact, flush thoroughly with water.

Stop use and ask doctor if irritation and redness develop and persists for more than 72 hours.

Keep out of reach of children. If swallowed, get medical help or contact a Poison Control Center right away.

Directions

- Dispense an adequate amount in your palm to cover all surfaces of hands completely.
- Rub hands together until dry.
- Supervise children in the use of this product.

Other Information

- Do not store above 100 ºF (38 ºC).
- May discolor some fabrics.

Inactive Ingredients

Water, Propylene Glycol, Triethanolamine, Carbomer, Glycerin

Questions or Comments?

1-319-455-3210 or www.b4brands.com